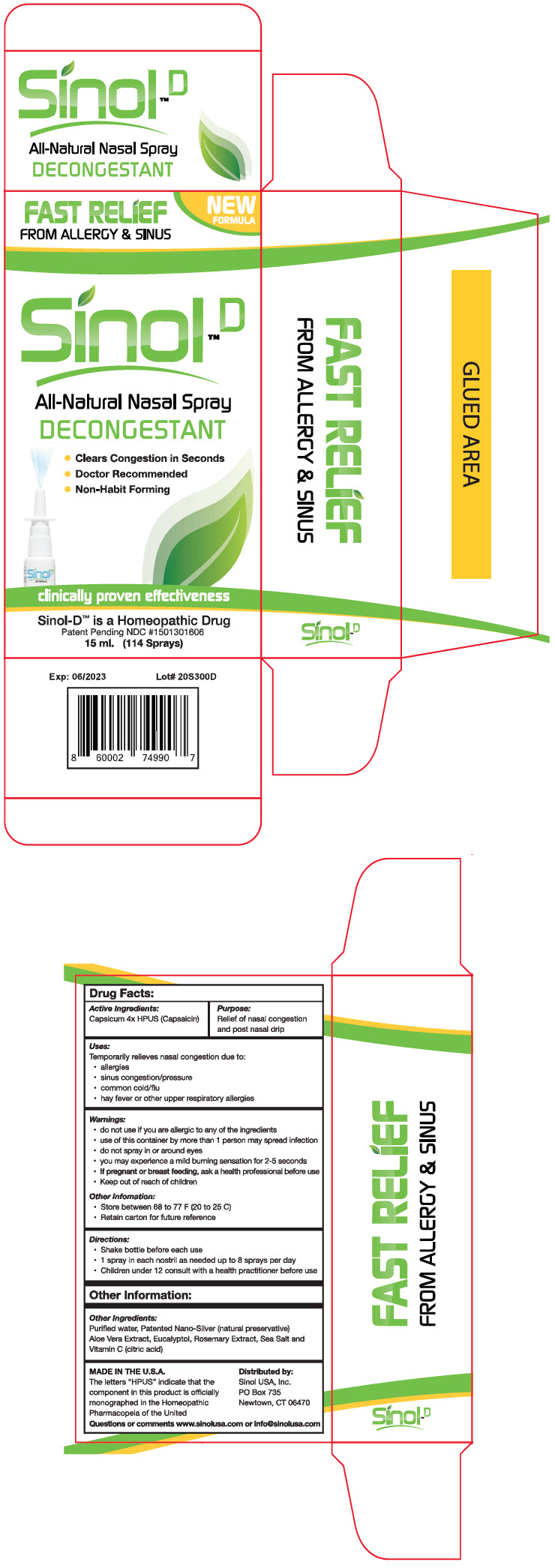 DRUG LABEL: SinolD 

NDC: 15013-016 | Form: SPRAY
Manufacturer: Sinol USA, Inc.
Category: homeopathic | Type: HUMAN OTC DRUG LABEL
Date: 20250129

ACTIVE INGREDIENTS: CAPSICUM 4 [hp_X]/0.263 mL
INACTIVE INGREDIENTS: WATER; SILVER; ALOE; EUCALYPTOL; ROSEMARY; SEA SALT; ASCORBIC ACID

Sinol™D
All-Natural Nasal Spray Decongestant

Drug Facts:

Active Ingredients

Capsicum 4× HPUS (Capsaicin)

Purpose

Relief of nasal congestion and post nasal drip

Uses

Temporarily relieves nasal congestion due to:

- allergies
- sinus congestion/pressure
- common cold/flu
- hay fever or other upper respiratory allergies

Warnings

- do not use if you are allergic to any of the ingredients

WHEN USING

- use of this container by more than 1 person may spread infection
- do not spray in or around eyes
- you may experience a mild burning sensation for 2-5 seconds

PREGNANCY OR BREAST FEEDING

- If pregnant or breast feeding, ask a health professional before use

- Keep out of reach of children

Other Information

- Store between 68 to 77 F (20 to 25 C)
- Retain carton for future reference

Directions

- Shake bottle before each use
- 1 spray in each nostril as needed up to 8 sprays per day
- Children under 12 consult with a health practitioner before use

Other Information

Other Ingredients

Purified water, Patented Nano-Silver (natural preservative) Aloe Vera Extract, Eucalyptol, Rosemary Extract, Sea Salt and Vitamin C (citric acid)

Questions or comments

www.sinolusa.com or info@sinolusa.com

Distributed by:
Sinol USA, Inc.
PO Box 735
Newtown, CT 06470

PRINCIPAL DISPLAY PANEL - 15 ml Bottle Carton

FAST RELIEF
FROM ALLERGY & SINUS

NEW
FORMULA

Sinol™D

All-Natural Nasal Spray
DECONGESTANT

- Clears Congestion in Seconds
- Doctor Recommended
- Non-Habit Forming

clinically proven effectiveness

Sinol-D™ is a Homeopathic Drug
Patent Pending NDC #1501301606
15 ml. (114 Sprays)